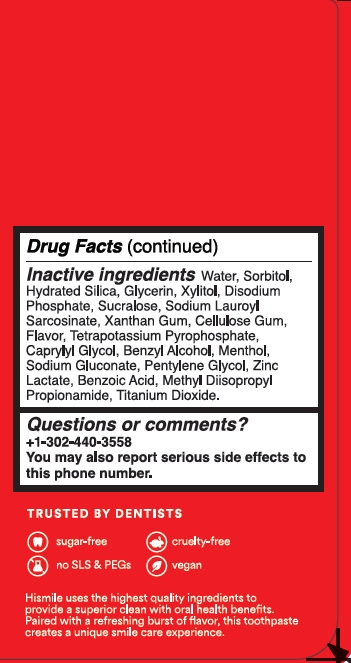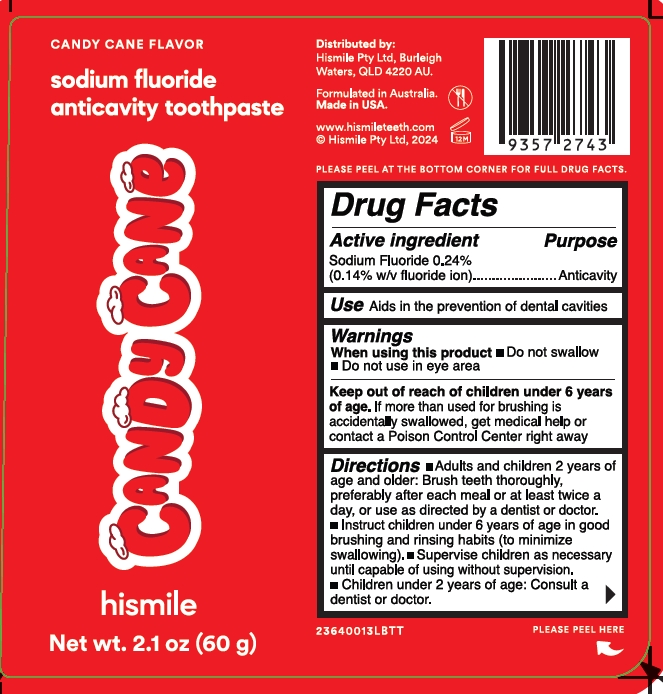 DRUG LABEL: Hismile
NDC: 83013-327 | Form: GEL
Manufacturer: HISMILE PTY LTD
Category: otc | Type: HUMAN OTC DRUG LABEL
Date: 20260115

ACTIVE INGREDIENTS: SODIUM FLUORIDE 0.243 g/100 g
INACTIVE INGREDIENTS: CARBOXYMETHYLCELLULOSE SODIUM, UNSPECIFIED FORM; XYLITOL; HYDRATED SILICA; SODIUM LAUROYL SARCOSINATE; GLYCERIN; CAPRYLYL GLYCOL; WATER; SORBITOL; XANTHAN GUM; SUCRALOSE; SODIUM GLUCONATE; ZINC LACTATE; METHYL DIISOPROPYL PROPIONAMIDE; PENTYLENE GLYCOL; BENZYL ALCOHOL; BENZOIC ACID; SODIUM PHOSPHATE, DIBASIC, ANHYDROUS; POTASSIUM PYROPHOSPHATE; MENTHOL; TITANIUM DIOXIDE

Candy Cane Flavor Sodium Fluoride Anticavity Toothpaste

Active ingredient

Sodium Fluoride 0.243%

(0.14 w/v fluoride ion)

Purpose

Anticavity

Use

Aids in the prevention of dental cavities

Warnings

When using this product

- Do not swallow
- Do not use in eye area

Keep out of reach of children under 6 years of age

If more than used for brushing is accidentally swallowed, get medical help or contact a Poison Control Center right away.

Directions

- Adults and children 2 years of age and older: Brush teeth thoroughly, preferably after each meal or at least twice a day, or use as directed by a dentist or doctor.
- Instruct children under 6 years of age in good brushing and rinsing habtis (to minimize swallowing).
- Supervise children as necessary until capable of using without supervision.
- Children under 2 years of age: Consult a dentist or doctor.

Inactive ingredients

Water

Sorbitol

Hydrated Silica

Glycerin

Xylitol

Disodium Phosphate

Sucralose

Sodium Lauroyl Sarcosinate

Xanthan Gum

Cellulose Gum

Flavor

Tetrapotassium Pyrophosphate

Caprylyl Glycol

Benzyl Alcohol

Menthol

Sodium Gluconate

Pentylene Glycol

Zinc Lactate

Benzoic Acid

Methyl Diisopropyl Propionamide

Titanium Dioxide